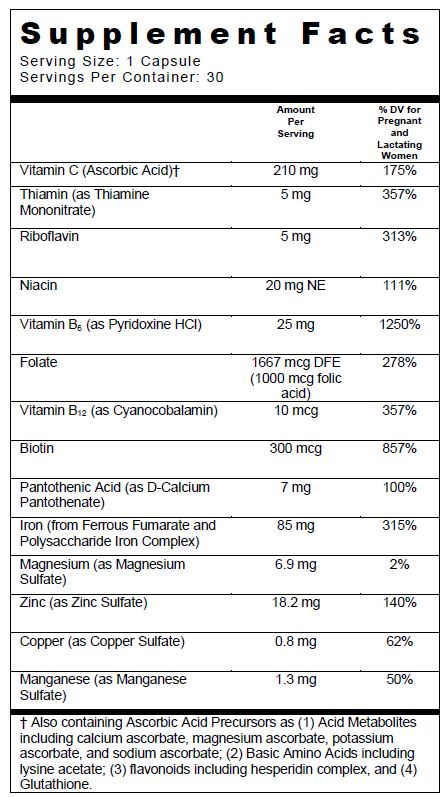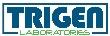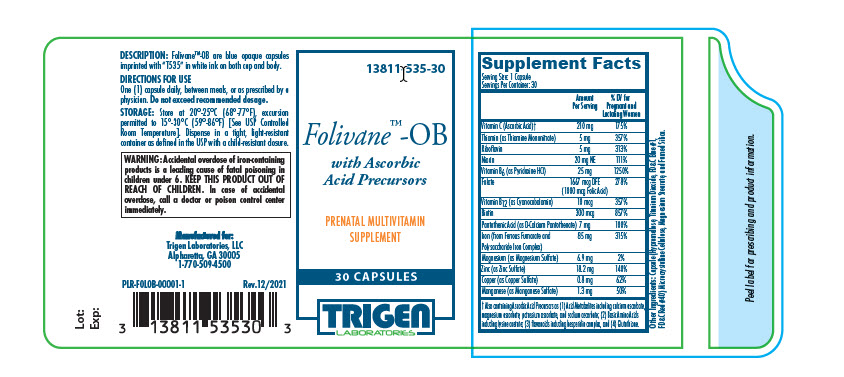 DRUG LABEL: Folivane-OB
NDC: 13811-535 | Form: CAPSULE
Manufacturer: Trigen Laboratories, LLC
Category: other | Type: DIETARY SUPPLEMENT
Date: 20220107

ACTIVE INGREDIENTS: Ferrous Fumarate 42.5 mg/1 1; Iron 42.5 mg/1 1; Ascorbic Acid 210 mg/1 1; Folic Acid 1 mg/1 1; Thiamine Mononitrate 5 mg/1 1; Riboflavin 5 mg/1 1; Niacin 20 mg/1 1; Calcium Pantothenate 7 mg/1 1; Pyridoxine Hydrochloride 25 mg/1 1; Biotin 300 ug/1 1; Cyanocobalamin 10 ug/1 1; Cupric Sulfate 800 ug/1 1; MAGNESIUM SULFATE HEPTAHYDRATE 6.9 mg/1 1; Manganese Sulfate 1.3 mg/1 1; Zinc Sulfate 18.2 mg/1 1
INACTIVE INGREDIENTS: Hypromelloses; Cellulose, Microcrystalline; Magnesium Stearate; Titanium Dioxide; FD&C Blue No. 1; FD&C Red No. 40; SILICON DIOXIDE

Folivane™-OB
Capsules

SUPPLEMENT FACTS

Other Ingredients: Capsule (Hypromellose, Titanium Dioxide, FD&C Blue #1, FD&C Red #40) Microcrystalline Cellulose, Magnesium Stearate, and Fumed Silica.

Folivane™-OB is a prescription prenatal supplement designed to improve the nutritional status of women throughout pregnancy and during the postnatal period to lactating and non-lactating mothers. Folivane™-OB may also be used to improve the nutritional status of women. DO NOT ADMINISTER TO CHILDREN UNDER THE AGE OF 12.

CONTRAINDICATIONS

Folivane™-OB is contraindicated in patients with known hypersensitivity to any of its ingredients; also, all iron compounds are contraindicated in patients with hemosiderosis, hemochromatosis, or hemolytic anemia. Pernicious anemia is a contraindication, as folic acid may obscure its signs and symptoms.

WARNING

WARNING: Accidental overdose of iron-containing products is a leading cause of fatal poisoning in children under 6. KEEP THIS PRODUCT OUTOF REACH OF CHILDREN. In case of accidental overdose, call a doctor or poison control center immediately.

PRECAUTION

General

Folic acid alone is improper therapy in the treatment of pernicious anemia and other megaloblastic anemias where B12 is deficient. Folic acid in doses above 0.1 mg daily may obscure pernicious anemia assessment, such that hematologic remission can occur while neurological manifestations remain progressive.

Biotin levels higher than the recommended daily allowance may cause interference with some laboratory tests, including cardiovascular diagnostic tests (e.g. troponin) and hormone test, and may lead to incorrect test results. Tell your healthcare provider about all prescription and over-the-counter medicines, vitamins, and dietary supplements that you take, including biotin.

Pediatric Use

Safety and effectiveness of this product have not been established in pediatric patients.

Geriatric Use

Safety and effectiveness of this product have not been established in elderly patients.

DRUG INTERACTIONS

Folivane™-OB is not recommended for and should not be given to patients receiving levodopa because the action of levodopa is antagonized by pyridoxine. There is a possibility of increased bleeding due to pyridoxine interaction with anticoagulants (e.g. Aspirin, Heparin, Clopidogrel).

ADVERSE REACTIONS

Folic Acid

Allergic sensitization have been reported following both oral and parenteral administration of folic acid.

Ferrous Fumarate

Gastrointestinal disturbances (anorexia, nausea, diarrhea, constipation) occur occasionally, but are usually mild and may subside with continuation of therapy. Although the absorption of iron is best when taken between meals, giving Folivane™-OB after meals may control occasional G.I. disturbances. Folivane™-OB is best absorbed when taken at bedtime.

OVERDOSAGE

Acute overdosage of iron may cause abdominal pain, nausea and vomiting and, in severe cases, cardiovascular collapse and death. Other more chronic symptoms include pallor and cyanosis, melena, shock, drowsiness and coma. The estimated overdose of orally ingested iron is 300 mg/kg body weight. Toxic effects are seen at 10-20 mg/kg elemental iron. When overdoses are ingested by children, severe reactions, including fatalities, have resulted. Folivane™-OB should be stored beyond the reach of children to prevent against accidental iron poisoning.

Treatment: For specific therapy, exchange transfusion and chelating agents should be used. For general management, perform gastric lavage with sodium bicarbonate solution or milk. Administer intravenous fluids and electrolytes and use oxygen.

DESCRIPTION

Folivane™-OB are blue opaque capsules imprinted with “T535” in white ink on both cap and body.

DIRECTIONS FOR USE

One (1) capsule daily, between meals, or as prescribed by a physician. Do not exceed recommended dosage.

HOW SUPPLIED

Folivane™-OB is dispensed in child-resistant bottles of 30 capsules.

Product Code: 13811-535-30

STORAGE

Store at 20°-25°C (68°-77°F), excursions permitted to 15°-30°C (59°-86°F) [See USP Controlled Room Temperature]. Dispense in a tight, light-resistant container as defined in the USP with a child-resistant closure.

KEEP OUT OF REACH OF CHILDREN.

HEALTH CLAIM

For use on the order of a healthcare practitioner.

Call your doctor about side effects. To report side effects, call Trigen Laboratories at 1-770-509-4500 or FDA at 1-800-FDA-1088.

PLR-FOLOB-00001-1 Rev. 12/2021

Manufactured for:
Trigen Laboratories, LLC
Alpharetta, GA 30005

1-770-509-4500

PRINCIPAL DISPLAY PANEL - 30 Capsule Bottle Label

13811-535-30

Folivane™-OB
with Ascorbic Acid Precursors

PRENATAL MULTIVITAMIN SUPPLEMENT

30 CAPSULES